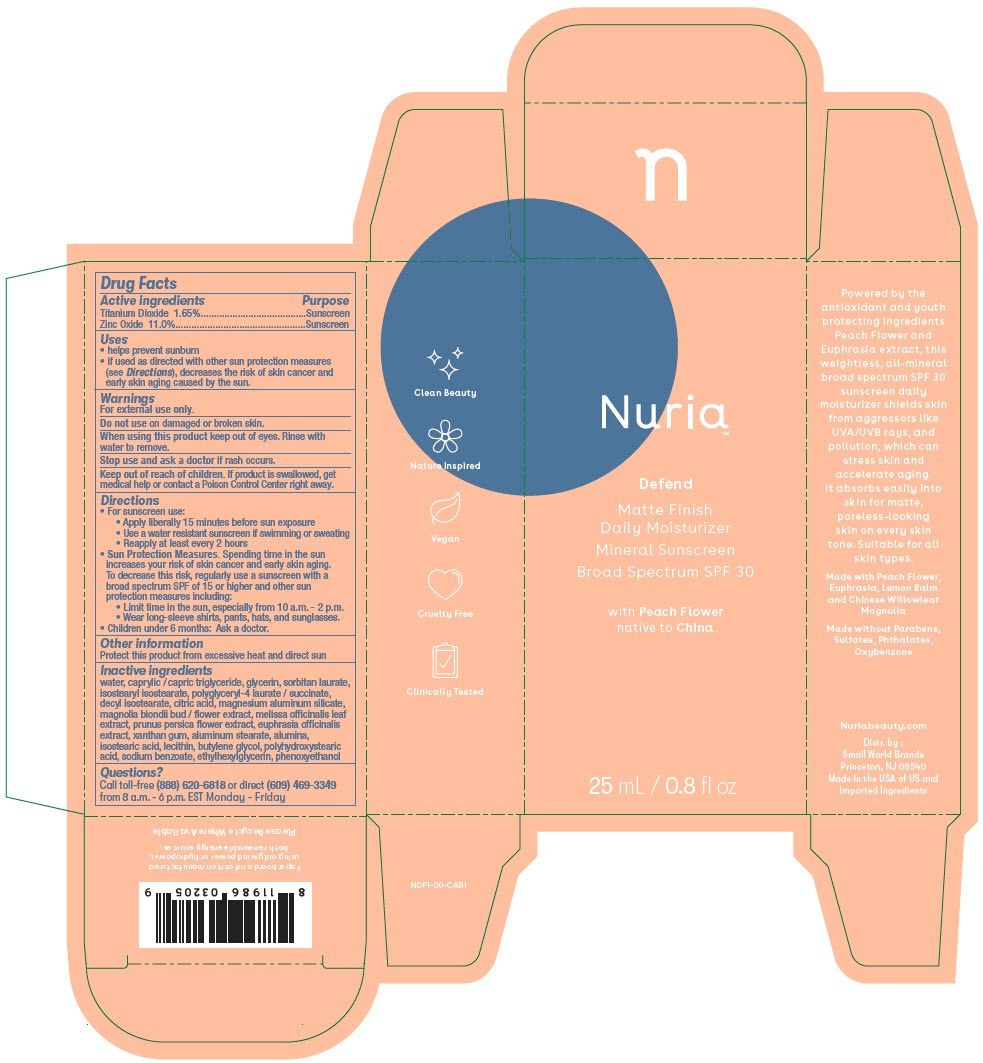 DRUG LABEL: Nuria Defend Matte Finish Daily Moisturizer Mineral Sunscreen Broad Spectrum SPF 30
NDC: 78611-4146 | Form: LOTION
Manufacturer: Small World Brands
Category: otc | Type: HUMAN OTC DRUG LABEL
Date: 20241220

ACTIVE INGREDIENTS: Titanium Dioxide 16.5 mg/1 mL; Zinc Oxide 110 mg/1 mL
INACTIVE INGREDIENTS: WATER; MEDIUM-CHAIN TRIGLYCERIDES; GLYCERIN; SORBITAN MONOLAURATE; ISOSTEARYL ISOSTEARATE; DECYL ISOSTEARATE; CITRIC ACID MONOHYDRATE; MAGNESIUM ALUMINUM SILICATE; MAGNOLIA BIONDII FLOWER BUD; MELISSA OFFICINALIS LEAF; PRUNUS PERSICA FLOWER; EUPHRASIA STRICTA; XANTHAN GUM; ALUMINUM STEARATE; ALUMINUM OXIDE; ISOSTEARIC ACID; SOYBEAN LECITHIN; BUTYLENE GLYCOL; POLYHYDROXYSTEARIC ACID STEARATE; SODIUM BENZOATE; ETHYLHEXYLGLYCERIN; PHENOXYETHANOL

Nuria Defend Matte Finish Daily Moisturizer Mineral Sunscreen Broad Spectrum SPF 30

Drug Facts

ACTIVE INGREDIENT

Active ingredients | Purpose
Titanium Dioxide 1.65% | Sunscreen
Zinc Oxide 11.0% | Sunscreen

Uses

- helps prevent sunburn
- if used as directed with other sun protection measures (see Directions), decreases the risk of skin cancer and early skin aging caused by the sun.

Warnings

For external use only.

Do not use on damaged or broken skin.

When using this product keep out of eyes. Rinse with water to remove.

Stop use and ask a doctor if rash occurs.

Keep out of reach of children. If product is swallowed, get medical help or contact a Poison Control Center right away.

Directions

- For sunscreen use:
  - Apply liberally 15 minutes before sun exposure
  - Use a water resistant sunscreen if swimming or sweating
  - Reapply at least every 2 hours
- Sun Protection Measures. Spending time in the sun increases your risk of skin cancer and early skin aging. To decrease this risk, regularly use a sunscreen with a broad spectrum SPF of 15 or higher and other sun protection measures including:
  - Limit time in the sun, especially from 10 a.m. - 2 p.m.
  - Wear long-sleeve shirts, pants, hats, and sunglasses.
- Children under 6 months: Ask a doctor.

Other information

Protect this product from excessive heat and direct sun

Inactive ingredients

water, caprylic / capric triglyceride, glycerin, sorbitan laurate, isostearyl isostearate, polyglyceryl-4 laurate / succinate, decyl isostearate, citric acid, magnesium aluminum silicate, magnolia biondii bud / flower extract, melissa officinalis leaf extract, prunus persica flower extract, euphrasia officinalis extract, xanthan gum, aluminum stearate, alumina, isostearic acid, lecithin, butylene glycol, polyhydroxystearic acid, sodium benzoate, ethylhexylglycerin, phenoxyethanol

Questions?

Call toll-free (888) 620-6818 or direct (609) 469-3349 from 8 a.m. - 6 p.m. EST Monday - Friday

Distr. by :
Small World Brands
Princeton, NJ 08540

PRINCIPAL DISPLAY PANEL - 25 mL Bottle Carton

Nuria™

Defend
Matte Finish
Daily Moisturizer
Mineral Sunscreen
Broad Spectrum SPF 30

with Peach Flower
native to China

25 mL / 0.8 fl oz